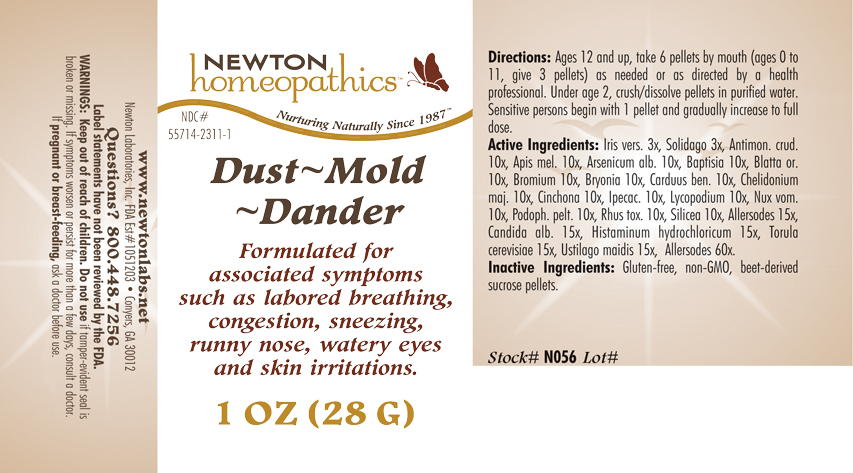 DRUG LABEL: Dust - Mold - Dander 
NDC: 55714-2311 | Form: PELLET
Manufacturer: Newton Laboratories, Inc.
Category: homeopathic | Type: HUMAN OTC DRUG LABEL
Date: 20110301

ACTIVE INGREDIENTS: Felis Catus Skin 60 [hp_X]/1 g; Canis Lupus Familiaris Skin 60 [hp_X]/1 g; Oryctolagus Cuniculus Skin 60 [hp_X]/1 g; Equus Caballus Skin 60 [hp_X]/1 g; Serinus Canaria Feather 60 [hp_X]/1 g; Gallus Gallus Feather 60 [hp_X]/1 g; Anas Platyrhynchos Feather 60 [hp_X]/1 g; Anser Anser Feather 60 [hp_X]/1 g; Melopsittacus Undulatus Feather 60 [hp_X]/1 g; Phasianus Colchicus Feather 60 [hp_X]/1 g; Meleagris Gallopavo Feather 60 [hp_X]/1 g; Felis Catus Hair 60 [hp_X]/1 g; Human Dander 60 [hp_X]/1 g; Canis Lupus Familiaris Hair 60 [hp_X]/1 g; Equus Caballus Hair 60 [hp_X]/1 g; Oryctolagus Cuniculus Hair 60 [hp_X]/1 g; Human Hair 60 [hp_X]/1 g; Human Skin 60 [hp_X]/1 g; Sheep Wool 60 [hp_X]/1 g; Bos Taurus Hair 60 [hp_X]/1 g; Capra Hircus Hair 60 [hp_X]/1 g; Cavia Porcellus Hair 60 [hp_X]/1 g; Mesocricetus Auratus Hair 60 [hp_X]/1 g; Wheat Gluten 15 [hp_X]/1 g; Aspergillus Niger Var. Niger 15 [hp_X]/1 g; Cladosporium Herbarum 15 [hp_X]/1 g; House Dust 15 [hp_X]/1 g; Candida Albicans 15 [hp_X]/1 g; Histamine Dihydrochloride 15 [hp_X]/1 g; Saccharomyces Cerevisiae 15 [hp_X]/1 g; Ustilago Maydis 15 [hp_X]/1 g; Antimony Trisulfide 10 [hp_X]/1 g; Apis Mellifera 10 [hp_X]/1 g; Arsenic Trioxide 10 [hp_X]/1 g; Baptisia Tinctoria Root 10 [hp_X]/1 g; Blatta Orientalis 10 [hp_X]/1 g; Bromine 10 [hp_X]/1 g; Bryonia Alba Root 10 [hp_X]/1 g; Centaurea Benedicta 10 [hp_X]/1 g; Chelidonium Majus 10 [hp_X]/1 g; Cinchona Officinalis Bark 10 [hp_X]/1 g; Ipecac 10 [hp_X]/1 g; Lycopodium Clavatum Spore 10 [hp_X]/1 g; Strychnos Nux-vomica Seed 10 [hp_X]/1 g; Podophyllum 10 [hp_X]/1 g; Toxicodendron Pubescens Leaf 10 [hp_X]/1 g; Silicon Dioxide 10 [hp_X]/1 g; Iris Versicolor Root 3 [hp_X]/1 g; Solidago Virgaurea Flowering Top 3 [hp_X]/1 g
INACTIVE INGREDIENTS: Sucrose

Dust - Mold - Dander

INDICATIONS & USAGE SECTION

Formulated for associated symptoms such as labored breathing, congestion, sneezing, runny nose, watery eyes and skin irritations.

DOSAGE & ADMINISTRATION SECTION

Directions: Ages 12 and up, take 6 pellets by mouth (ages 0 to 11, give 3 pellets) as needed or as directed by a health professional. Under age 2, crush/dissolve pellets in purified water. Sensitive persons begin with 1 pellet and gradually increase to full dose.

OTC - ACTIVE INGREDIENT SECTION

Allersodes 60x, Allersodes 15x, Candida alb. 15x, Histaminum hydrochloricum 15x, Torula cerevisiae 15x, Ustilago maidis 15x, Antimon. crud. 10x, Apis mel. 10x, Arsenicum alb. 10x, Baptisia 10x, Blatta or. 10x, Bromium 10x, Bryonia 10x, Carduus ben. 10x, Chelidonium maj. 10x, Cinchona 10x, Ipecac. 10x, Lycopodium 10x, Nux vom. 10x, Podoph. pelt. 10x, Rhus tox. 10x, Silicea 10x, Iris versicolor 3x, Solidago 3x.

OTC - PURPOSE SECTION

Formulated for associated symptoms such as labored breathing, congestion, sneezing, runny nose, watery eyes and skin irritations.

INACTIVE INGREDIENT SECTION

Inactive Ingredients: Gluten-free, non-GMO, beet-derived sucrose pellets.

QUESTIONS SECTION

www.newtonlabs.net Newton Laboratories, Inc. FDA Est # 1051203 - Conyers, GA 30012
Questions? 1.800.448.7256

WARNINGS SECTION

Warning: Keep out of reach of children. Do not use if tamper-evident seal is broken or missing. If symptoms worsen or persist for more than a few days, consult a doctor. If pregnant or breast-feeding, ask a doctor before use.

OTC - PREGNANCY OR BREAST FEEDING SECTION

If pregnant or breast-feeding, ask a doctor before use.

OTC - KEEP OUT OF REACH OF CHILDREN SECTION

Keep out of reach of children.